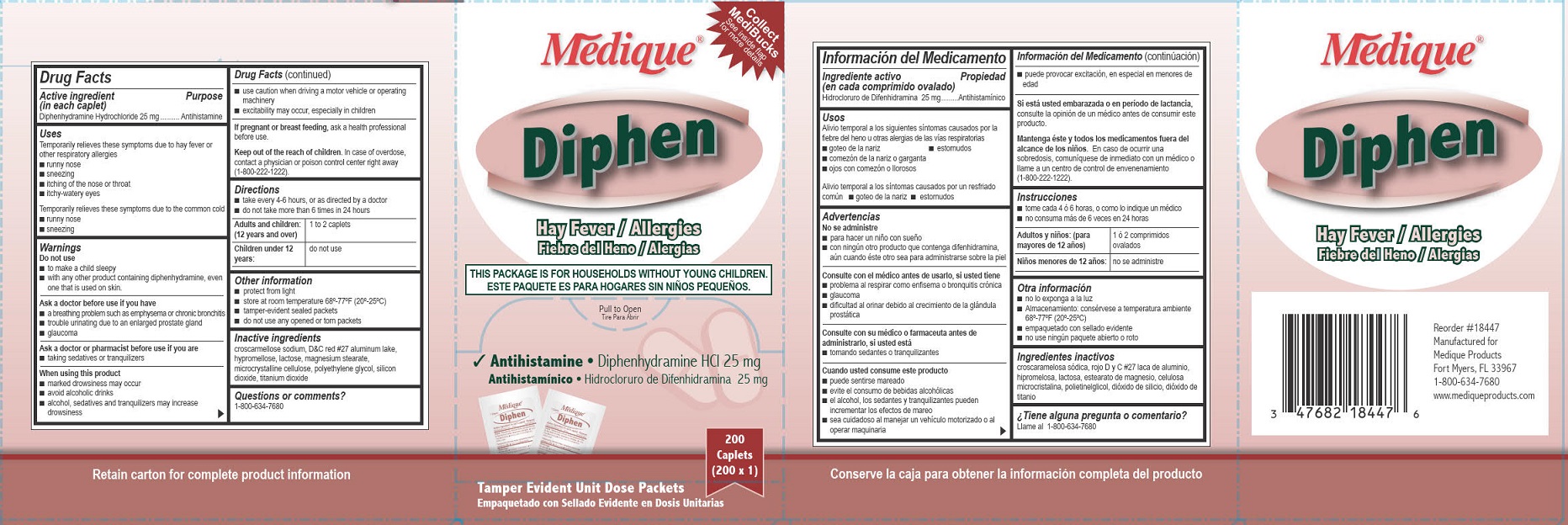 DRUG LABEL: Medique Diphen
NDC: 47682-167 | Form: TABLET, FILM COATED
Manufacturer: Unifirst First Aid Corporation
Category: otc | Type: HUMAN OTC DRUG LABEL
Date: 20250908

ACTIVE INGREDIENTS: DIPHENHYDRAMINE HYDROCHLORIDE 25 mg/1 1
INACTIVE INGREDIENTS: CELLULOSE, MICROCRYSTALLINE; CROSCARMELLOSE SODIUM; D&C RED NO. 27; HYPROMELLOSES; LACTOSE; MAGNESIUM STEARATE; POLYETHYLENE GLYCOL, UNSPECIFIED; SILICON DIOXIDE; TITANIUM DIOXIDE

Medique Diphen

Drug Facts

Active ingredient (in each caplet)

Diphenhydramine HCl 25 mg

Purpose

Antihistamine

Uses

Temporarily relieves these symptoms due to hay fever or other respiratory allergies

- runny nose
- sneezing
- itching of the nose or throat
- itchy-watery eyes

Temporarily relieves these symptoms due to the common cold

- runny nose
- sneezing

Warnings

Do not use

- to make a child sleepy
- with any other product containing diphenhydramine, even one that is used on skin.

Ask a doctor before use if you have

■ a breathing problem such as emphysema or chronic bronchitis

■ trouble urinating due to an enlarged prostate gland

■ glaucoma

Ask a doctor or pharmacist before use if you are

- taking sedatives or tranquilizers

When using this product

- marked drowsiness may occur
- avoid alcohol beverages
- alcohol, sedatives and tranquilizers may increase drowsiness
- use caution when driving a motor vehicle or operating machinery
- excitability may occur, especially in children

PREGNANCY OR BREAST FEEDING

If pregnant or breast feeding, ask a health professional before use.

Keep out of the reach of children.

In case of overdose, contact a physician or poison control center right away (1-800-222-1222).

Directions

- take every 4-6 hours, or as directed by a doctor
- do not take more than 6 times in 24 hours

Adults and children: (12 years and over) 1 to 2 caplets

Children under 12 years: do not use

Other information

- store at room temperature 68º-77ºF (20º-25ºC)
- protect from light
- tamper-evident sealed packets
- do not use any opened or torn packets

Inactive ingredients

croscarmellose sodium, D&C red #27 aluminum lake, hypromellose, lactose, magnesium stearate, microcrystalline cellulose, polyethylene glycol, silicon dioxide, titanium dioxide

Questions or comments? 1-800- 634-7680

184R Medique Diphen Label

Collect MediBucks See inside flap for more details

Medique®

Diphen

Hay Fever / Allergies

Fiebre del Heno / Alergias

This Package is for Households without Young Children.

Este Paquete Es Para Hogares Sin Ninos Pequenos.

Antihistamine • Diphenhydramine HCl 25 mg

Antihistaminico • Hidrocloruro de Difenhidramina 25mg

200 Caplets

(200 x 1)

Tamper Evident Unit Dose Packets

Empaquetado con Sellado Evidente en Dosis Unitarias

Medique 167 Diphen Principal Display Panel

Collect MediBucks See inside flap for more details

Medique®

Diphen

Hay Fever / Allergies

Fiebre del Heno / Alergias

This Package is for Households without Young Children.

Este Paquete Es Para Hogares Sin Ninos Pequenos.

Antihistamine • Diphenhydramine HCl 25 mg

Antihistaminico • Hidrocloruro de Difenhidramina 25mg

200 Caplets

(200 x 1)

Tamper Evident Unit Dose Packets

Empaquetado con Sellado Evidente en Dosis Unitarias